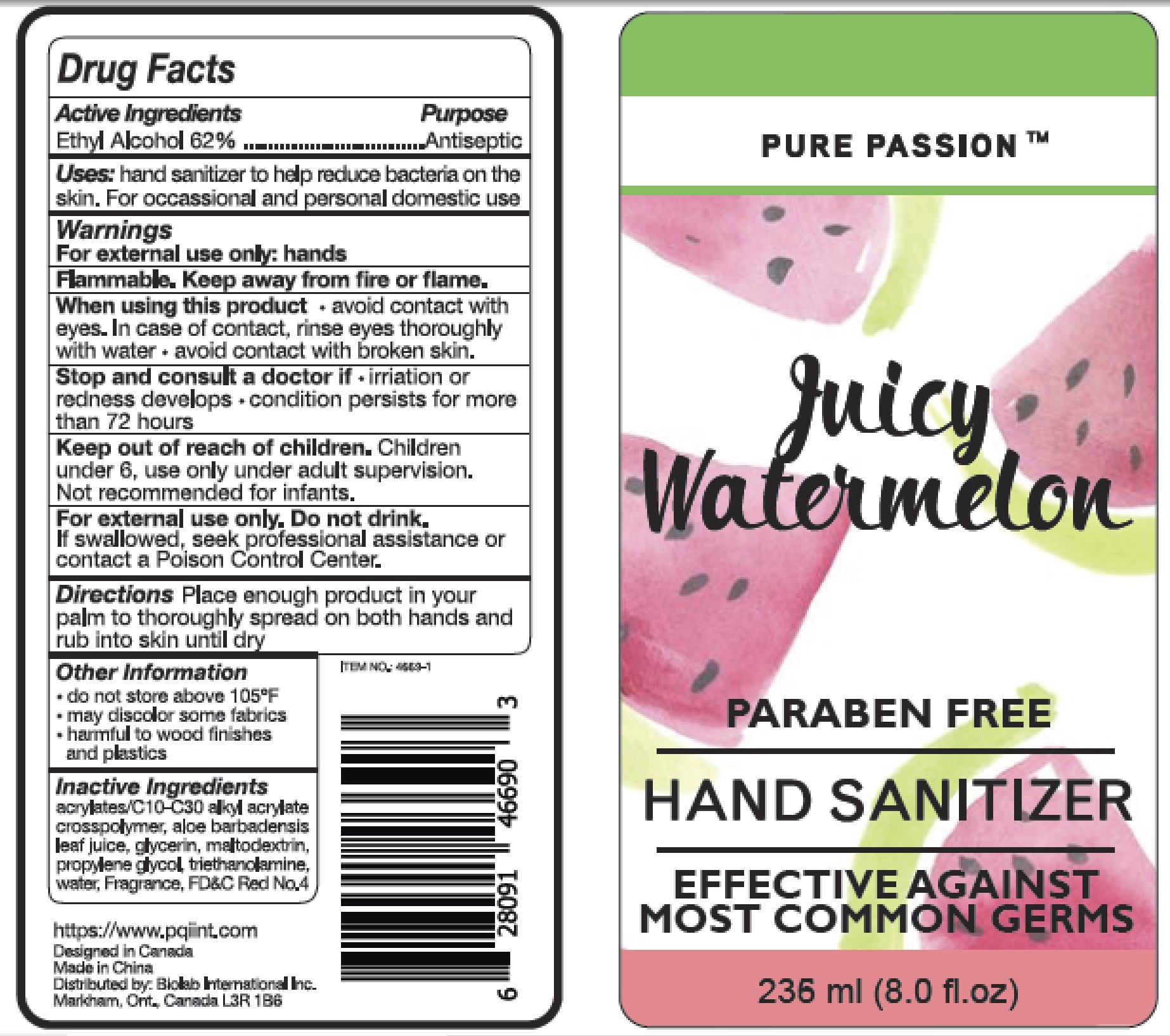 DRUG LABEL: Hand Sanitizer
NDC: 72264-028 | Form: GEL
Manufacturer: Biolab International Incorporated
Category: otc | Type: HUMAN OTC DRUG LABEL
Date: 20200630

ACTIVE INGREDIENTS: ALCOHOL 62 mL/100 mL
INACTIVE INGREDIENTS: TROLAMINE; MALTODEXTRIN; PROPYLENE GLYCOL; WATER; ALOE VERA LEAF; GLYCERIN; CARBOMER INTERPOLYMER TYPE A (55000 CPS); FD&C RED NO. 4

Active ingredients

Ethyl Alcohol 62%

Purpose
Antiseptic

INDICATIONS AND USAGE

Uses hand sanitizer to help reduce bacteria on the skin . For occassional and personal domestic use

Warnings

for external use only: hands

Flammable. Keep away from fire or flame

when using this product, avoid contact with eyes, in case of contact, rinse eyes thoroughly with water, avoid contact with broken skin .

Stop use and consult a doctor if . irritation or redness develops. condition persists for more than 72 hours

Keep out of reach of children. children under 6, use only under adult supervision, Not recommended for infants.

For external use only. Do not drink.
If swallowed, seek professional assistance or contact a poison control center.

DOSAGE AND ADMINISTRATION

Directions. Place enough product in your palm to thoroughly spread on both hands and rub into skin until dry.

Other information. do not store above 105°F， may discolor some fabics. harmful to wood finished and plastics

INACTIVE INGREDIENT

Inactive ingredients acrylates/C10-C30 alkyl acrylate crosspolymer,aloe barbadensis leaf juice, glycerin, maltodextrin, propylene glycol, water , triethanolamine,Fragrance. FD&C Red No.4